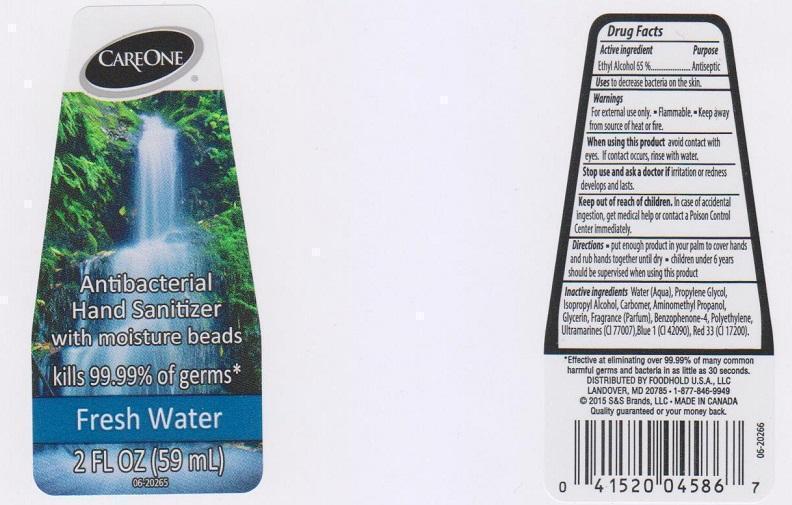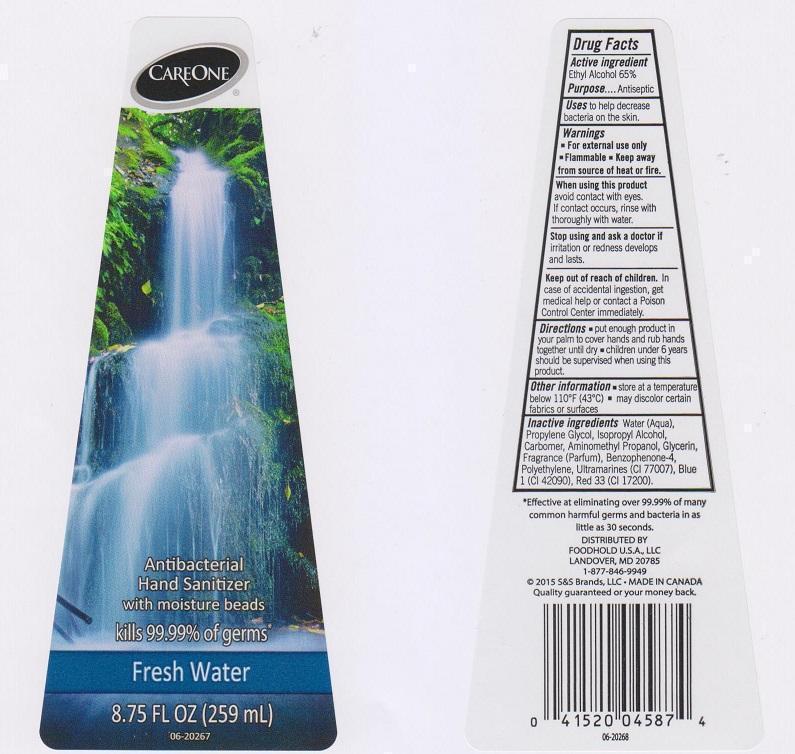 DRUG LABEL: CAREONE
NDC: 41520-412 | Form: LIQUID
Manufacturer: AMERICAN SALES COMPANY
Category: otc | Type: HUMAN OTC DRUG LABEL
Date: 20150304

ACTIVE INGREDIENTS: ALCOHOL 650 mg/1 mL
INACTIVE INGREDIENTS: WATER; PROPYLENE GLYCOL; ISOPROPYL ALCOHOL; CARBOMER 934; AMINOMETHYLPROPANOL; GLYCERIN; SULISOBENZONE; HIGH DENSITY POLYETHYLENE; ULTRAMARINE BLUE; FD&C BLUE NO. 1; D&C RED NO. 33

DRUG FACTS

ACTIVE INGREDIENT

ETHYL ALCOHOL 65%

PURPOSE

ANTISEPTIC

USES

TO HELP DECREASE BACTERIA ON THE SKIN

WARNINGS

FOR EXTERNAL USE ONLY

- FLAMMABLE
- KEEP AWAY FROM SOURCE OF HEAT OR FIRE

WHEN USING THIS PRODUCT

AVOID CONTACT WITH EYES. IF CONTACT OCCURS, RINSE WITH THOROUGHLY WITH WATER

STOP USING AND ASK A DOCTOR IF

IRRITATION OR REDNESS DEVELOPS AND LASTS

KEEP OUT OF REACH OF CHILDREN

IN CASE OF ACCIDENTAL INGESTION, GET MEDICAL HELP OR CONTACT A POISON CONTROL CENTER IMMEDIATELY

DIRECTIONS

- PUT ENOUGH PRODUCT IN YOUR PALM TO COVER HANDS AND RUB HAND TOGETHER UNTIL DRY
- CHIDREN UNDER 6 YEARS SHOULD BE SUPERVISED WHEN USING THIS PRODUCT

OTHER INFORMATION

- STORE AT A TEMPERATURE BELOW 110°F (43°C)
- MAY DISCOLOR CERTAIN FABRICS OR SURFACES

INACTIVE INGREDIENTS

WATER (AQUA), PROPYLENE GLYCOL, ISOPROPYL ALCOHOL, CARBOMER, AMINOMETHYL PROPANOL, GLYCERIN, FRAGRANCE (PARFUM), BENZOPHENONE-4, POLYETHYLENE, ULTRAMARINES (CI 77007), BLUE 1 (CI 42090), RED 33 (CI 17200)